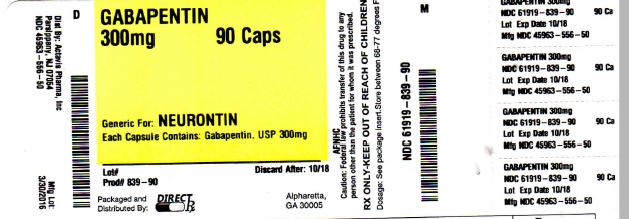 DRUG LABEL: GABAPENTIN
NDC: 61919-839 | Form: CAPSULE
Manufacturer: DIRECT RX
Category: prescription | Type: HUMAN PRESCRIPTION DRUG LABEL
Date: 20160331

ACTIVE INGREDIENTS: GABAPENTIN 300 mg/1 1
INACTIVE INGREDIENTS: FERRIC OXIDE YELLOW; FERROSOFERRIC OXIDE; STARCH, CORN; D&C YELLOW NO. 10; FD&C BLUE NO. 1; SODIUM LAURYL SULFATE; FD&C RED NO. 40; FD&C BLUE NO. 2; GELATIN; MANNITOL; PROPYLENE GLYCOL; FERRIC OXIDE RED; SILICON DIOXIDE; TALC; TITANIUM DIOXIDE; SHELLAC

GABAPENTIN 300mg 90CAPS